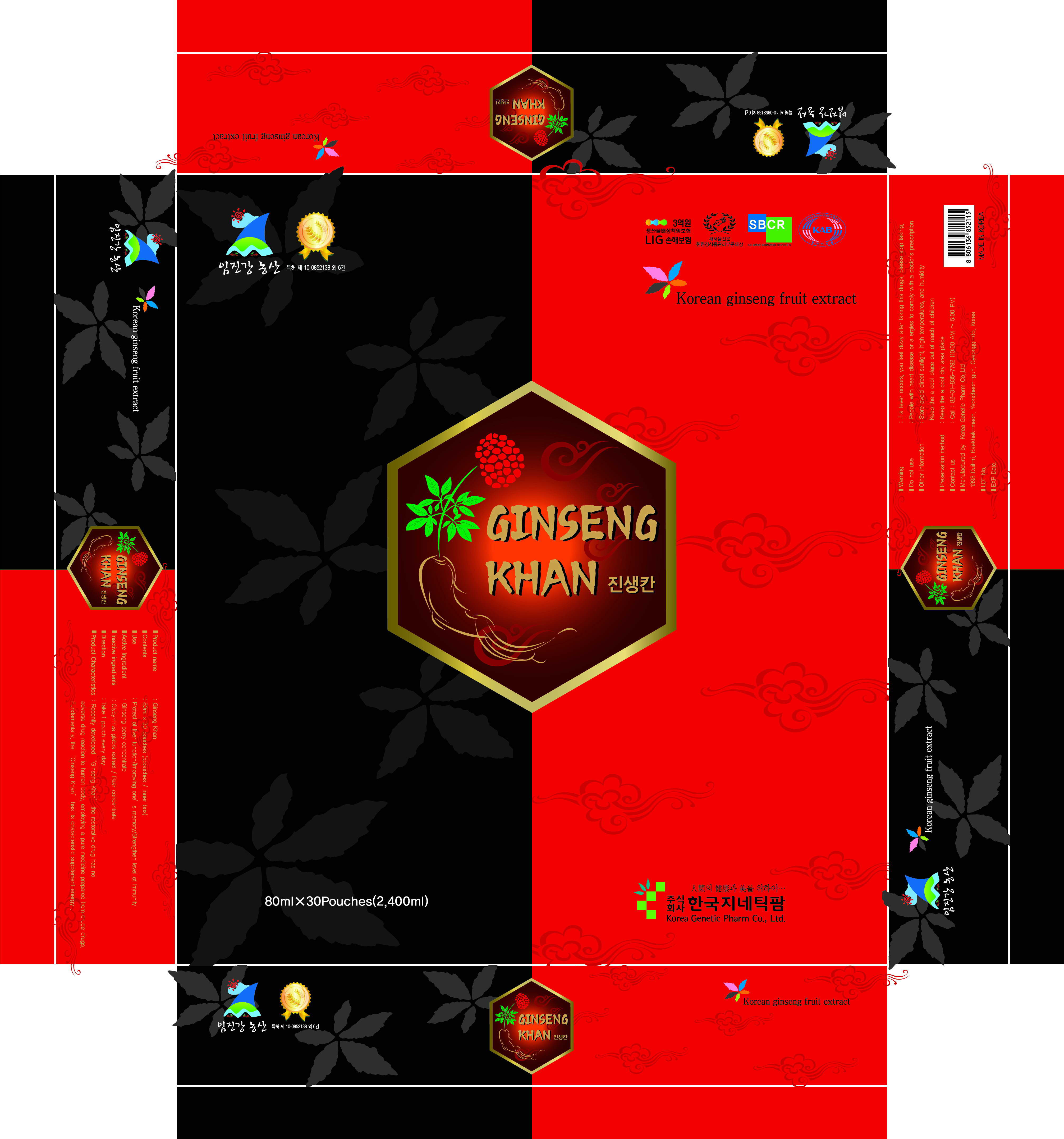 DRUG LABEL: Ginseng Khan
NDC: 42707-3001 | Form: LIQUID
Manufacturer: Korea Genetic Pharm Co., Ltd 
Category: otc | Type: HUMAN OTC DRUG LABEL
Date: 20120215

ACTIVE INGREDIENTS: PANAX GINSENG FRUIT 90 mL/100 mL
INACTIVE INGREDIENTS: GLYCYRRHIZA GLABRA; PEAR JUICE

Drug Facts

active ingredient: ginseng berry concentrate

inactive ingredient: glycyrrhiza glabra extract, pear concentrate

PURPOSE

protect of liver function, improving one's memory, strengthen level of immunity

keep out of reach of the children

INDICATIONS AND USAGE

take one pouch daily

WARNINGS

if a fever occurs or you feel dizzy after taking this drugs, immediately stop taking

DOSAGE AND ADMINISTRATION

people with heart disease or allergies to comply with a doctor's prescription